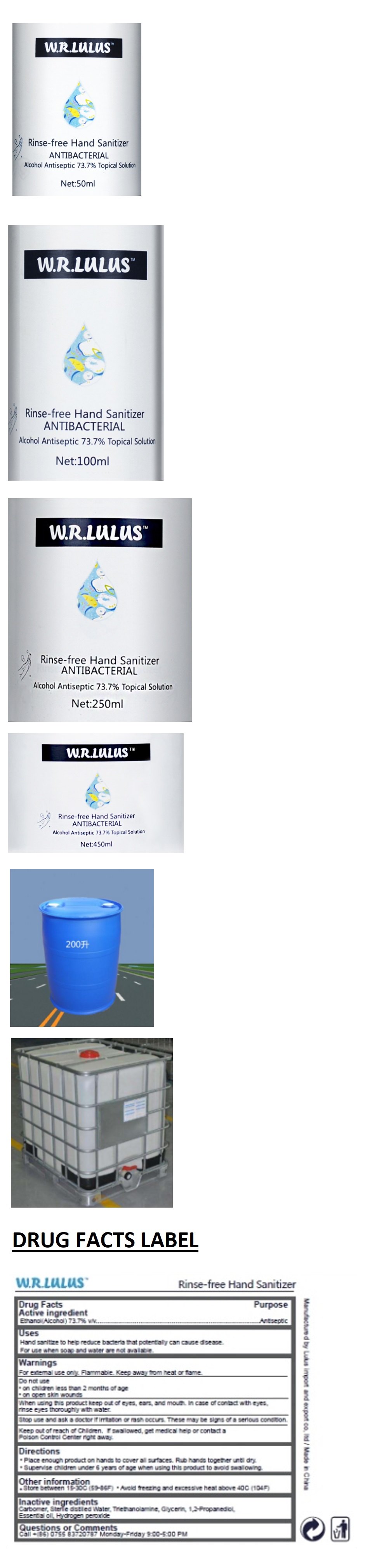 DRUG LABEL: W.R.LULUS Rinse-free Hand Sanitizer
NDC: 77335-001 | Form: SOLUTION
Manufacturer: Lulus import and export co., ltd
Category: otc | Type: HUMAN OTC DRUG LABEL
Date: 20200525

ACTIVE INGREDIENTS: ALCOHOL 73.7 L/100 L
INACTIVE INGREDIENTS: CARBOMER HOMOPOLYMER, UNSPECIFIED TYPE; WATER; TROLAMINE; GLYCERIN; PROPYLENE GLYCOL; HYDROGEN PEROXIDE

W.R.LULUSTM Rinse-free Hand Sanitizer

Active ingredient

Ethanol (Alcohol) 73.7% v/v

Purpose

Antiseptic

Uses

Hand sanitize to help reduce bacteria that potentially can cause disease.

For use when soap and water are not available.

Warnings

For external use only. Flammable. Keep away from fire or flame.

Do not use

- on children less than 2 months of age
- on open skin wounds

When using this product keep out of eyes, ears, and mouth. In case of contact with eyes, rinse eyes thoroughly with water.

Stop use and ask a doctor if irritation or rash occurs. These may be signs of a serious condition.

Keep out of reach of Children. If swallowed, get medical help or contact a Poison Control Center right away.

Directions

- Place enough product on hands to cover all surfaces. Rub hands together until dry.
- Supervise children under 6 years of age when using this product to avoid swallowing.

Other information

• Store between 15-30C (59 - 86F). • Avoid freezing and excessive heat above 40C (104F)

Inactive ingredients

Carbomer, Sterile distilled Water, Triethanolamine, Glycerin, 1,2-Propanediol, Essential oil, Hydrogen peroxide

Questions or Comments

Call +(86) 0755 83720787 Monday-Friday 9:00-5:00 PM

ANTIBACTERIAL

Alcohol Antispetic 73.7% Topical Solution

Manufactured by Lulus import and expot co. ltd / Made in China